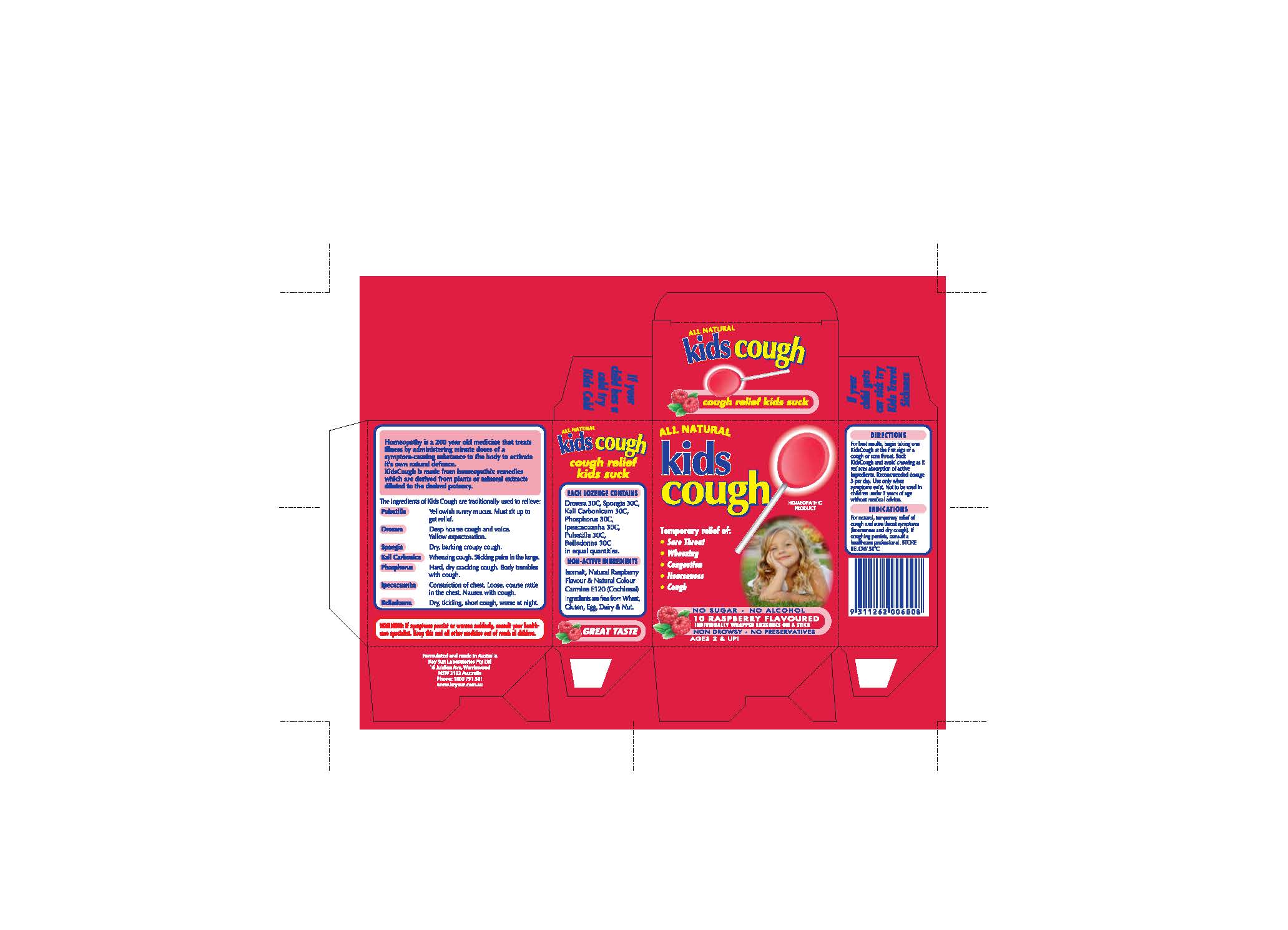 DRUG LABEL: kids cough
                
                
NDC: 64997-180 | Form: LOZENGE
Manufacturer: KEYSUN PTY. LIMITED Also Traded as KEYSUN LABORATORIES
Category: homeopathic | Type: HUMAN OTC DRUG LABEL
Date: 20140513

ACTIVE INGREDIENTS: DROSERA INTERMEDIA 30 [hp_X]/1 1; SPONGIA OFFICINALIS WHOLE 30 [hp_X]/1 1; POTASSIUM CARBONATE 30 [hp_X]/1 1; PHOSPHORUS 30 [hp_X]/1 1; PULSATILLA VULGARIS 30 [hp_X]/1 1; ATROPA BELLADONNA 30 [hp_X]/1 1; IPECAC 30 [hp_X]/1 1
INACTIVE INGREDIENTS: ISOMALT; COCHINEAL

Homeopathic Drug Facts

INACTIVE INGREDIENT

Non-Active Ingredients

Isomalt, Natural Raspberry Flavour and Natural Colour Carmine E120 (Cochineal)

ACTIVE INGREDIENT

Each lozenge contains:

Drosera 30C, Spongia 30C,

Kali Carbonicum 30C,

Phospherous 30C, Ipeacacuanha 30C,

Pulsatilla 30C, Belladonna 30C

in equal quantities.

PURPOSE

Indications

For natural, temporary relief of

cough and sore throat symptoms

(hoarseness and dry cough)

WARNINGS

Warning: If symptoms persist or worsen suddenly, consult your

healthcare specialist.

KEEP OUT OF REACH OF CHILDREN

Keep this and all other medicines out of reach of children.

Directions

For best results, begin taking one

KidsCough at the first sign of a cough or sore throat.

Suck KidsCough and avoid chewing as it reduces

absorption of active ingredients. Recommended dosage

3 per day. Use only when symptoms exist. Not to be used

in children under 2 years of age without medical advice.

Indications

For natural, temporary relief of

cough and sore throat symptoms

(hoarseness and dry cough). If

coughing persists, consult a healthcare professional.

STORAGE AND HANDLING

STORE BELOW 30 C